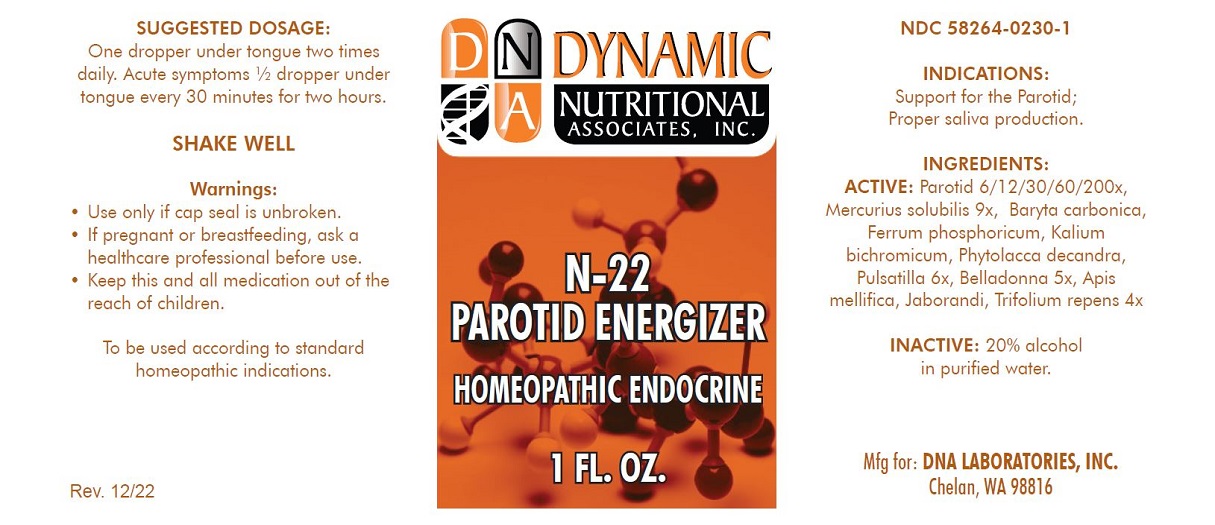 DRUG LABEL: N-22
NDC: 58264-0230 | Form: SOLUTION
Manufacturer: DNA Labs, Inc.
Category: homeopathic | Type: HUMAN OTC DRUG LABEL
Date: 20221229

ACTIVE INGREDIENTS: MERCURIUS SOLUBILIS 9 [hp_X]/1 mL; BARIUM CARBONATE 6 [hp_X]/1 mL; ATROPA BELLADONNA 5 [hp_X]/1 mL; POTASSIUM DICHROMATE 6 [hp_X]/1 mL; PHYTOLACCA AMERICANA WHOLE 6 [hp_X]/1 mL; ANEMONE PULSATILLA 6 [hp_X]/1 mL; BOS TAURUS PAROTID GLAND 200 [hp_X]/1 mL; APIS MELLIFERA 4 [hp_X]/1 mL; PILOCARPUS MICROPHYLLUS LEAF 4 [hp_X]/1 mL; FERROSOFERRIC PHOSPHATE 6 [hp_X]/1 mL; TRIFOLIUM REPENS WHOLE 4 [hp_X]/1 mL
INACTIVE INGREDIENTS: ALCOHOL; WATER

N-22

NDC 58264-0230-1

INDICATIONS AND USAGE

PURPOSE

Support for the Parotid; Proper saliva production

ACTIVE INGREDIENT

Parotid 6/12/30/60/200x, Mercurius solubilis 9x, Baryta carbonica, Ferrum phosphoricum, Kalium bichromicum, Phytolacca decandra, Pulsatilla 6x, Belladonna 5x, Apis mellifica, Jaborandi, Trifolium repens 4x

INACTIVE INGREDIENT

20% alcohol in purified water.

DOSAGE AND ADMINISTRATION

One dropper under tongue two times daily. Acute symptoms 1/2 dropper under tongue every 30 minutes for two hours.

STORAGE AND HANDLING

SHAKE WELL

WARNINGS

Use only if cap seal is unbroken.

PREGNANCY OR BREAST FEEDING

If pregnant or breastfeeding, ask a healthcare professional before use.

KEEP OUT OF REACH OF CHILDREN

Keep this and all medication out of the reach of children.

To be used according to standard homeopathic indications.

PACKAGE LABEL

DYNAMIC

NUTRITIONAL

ASSOCIATES, INC.

N-22

PAROTID ENERGIZER

HOMEOPATHIC ENDOCRINE

1 FL. OZ.